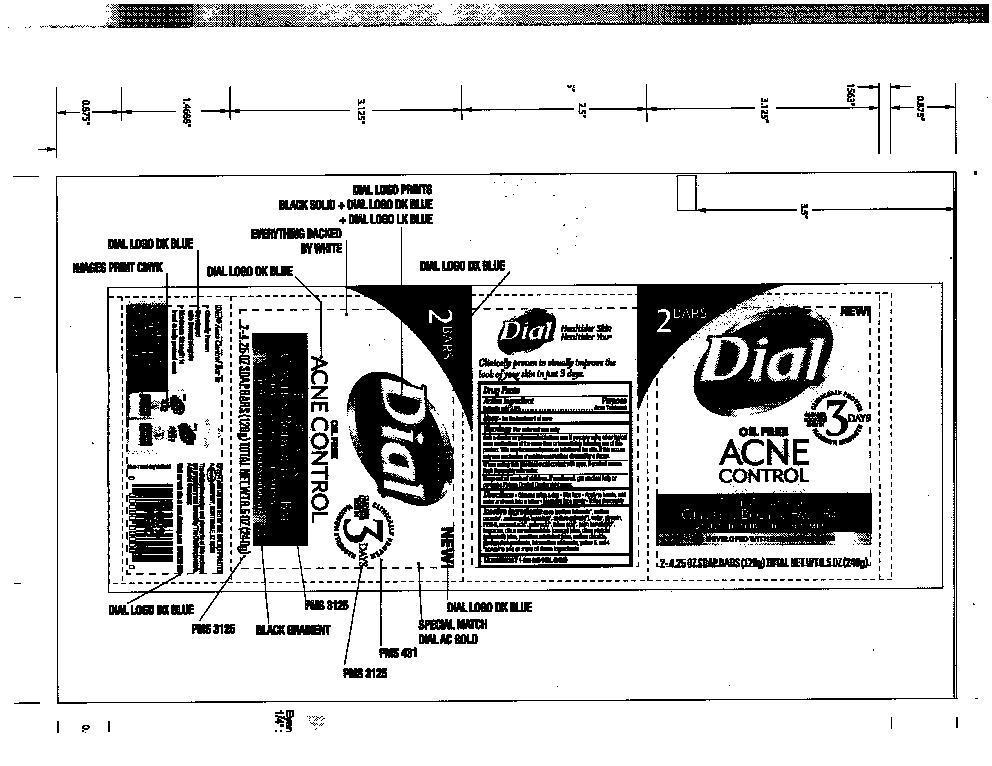 DRUG LABEL: Dial Acne
NDC: 51815-307 | Form: SOAP
Manufacturer: VVF Illinois Services LLC
Category: otc | Type: HUMAN OTC DRUG LABEL
Date: 20140606

ACTIVE INGREDIENTS: SALICYLIC ACID 4.8 g/240 g
INACTIVE INGREDIENTS: SODIUM TALLOWATE, BEEF; SODIUM COCOATE; SODIUM PALM KERNELATE; SODIUM PALMATE; Water; GLYCERIN; PROPYLENE GLYCOL; COCONUT ACID; PALM ACID; TALLOW ACID, BEEF; PALM KERNEL ACID; CITRUS AURANTIUM FRUIT OIL; CITRUS PARADISI FRUIT OIL; PASSIFLORA EDULIS FRUIT JUICE; SODIUM CHLORIDE; PENTASODIUM PENTETATE; ETIDRONATE TETRASODIUM; FD&C YELLOW NO. 5; FD&C RED NO. 4

Dial Acne

ACTIVE INGREDIENT

Salicylic acid

PURPOSE

Acne Treatment

KEEP OUT OF REACH OF CHILDREN

If swallowed, get medical

help or contact Poison Control right away.

USE

For the treatment of acne

WARNINGS

For external use only, avoid contact with eyes. If contact occurs flush thoroughly with water.

USE

wet bar with water - lather vigorously -

and wash skin - rinse and dry thoroughly

QUESTIONS

1-800-258 (DIAL)

Inactive ingredients

Soap (sodium tallowate, sodium cocoate, sodium palm kernelate, sodium palmate), water, glycerin, PEG-8, coconut acid, palm acid, tallow acid, palm kernel acid, fragrance, citrus aurantium dulcis (orange) juice, citrus paradisi (grapefruit) juice, passiflora edulis fruit juice, sodium chloride, pentasodium pentetate, Tetrasodium etidronate, yellow 5, red 4